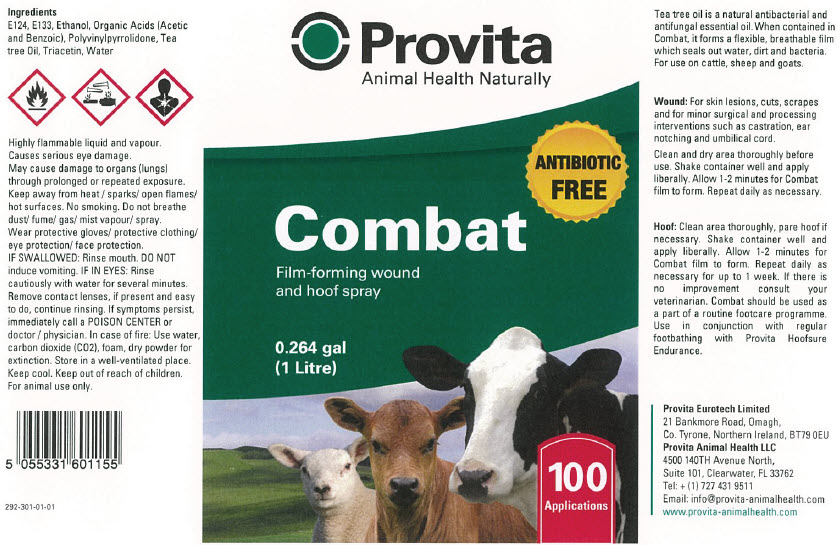 DRUG LABEL: Provita 
NDC: 16371-101 | Form: SPRAY
Manufacturer: Provita Eurotech Ltd
Category: animal | Type: OTC ANIMAL DRUG LABEL
Date: 20230811

ACTIVE INGREDIENTS: BENZOIC ACID 74 g/1 L

Combat

Ingredients

E124, E133, Ethanol, Organic Acids (Acetic and Benzoic),Polyvinylpyrrolidone, Tea tree Oil, Triacetin, Water

WARNINGS

Danger: Flammable liquid and vapour. Harmful if swallowed. Keep away from heat/ sparks/open flames/hotsurfaces — No smoking. Do not breathe dust / fume / gas / mist / vapours / spray. Wear protective gloves/ protective clothing/eye protection/face protection. IF SWALLOWED: Rinse mouth. Do NOT induce vomiting. IF IN EYES: Rinse cautiously with water for several minutes. Remove contact lenses, if present and easy to do, continue rinsing. If symptoms persist, immediately call a POISON CENTER or doctor/physician. In case of fire: Use water, carbon dioxide (CO2), foam, dry powder for extinction. Store in a well-ventilated place. Keep cool. Keep out of reach of children.

For animal use only.

Tea tree oil is a natural antibacterial and antifungal essential oil. When contained in Combat, it forms a flexible, breathable film which seals out water, dirt and bacteria. For use on cattle, sheep and goats.

DOSAGE AND ADMINISTRATION

Wound: For skin lesions, cuts, scrapes and for minor surgical and processing interventions such as castration, ear notching and umbilical cord. Clean and dry area thoroughly before use. Shake container well and apply liberally. Allow 1-2 minutes for Combat film to form. Repeat daily as necessary.

DOSAGE AND ADMINISTRATION

Hoof: Clean area thoroughly, pare hoof if necessary. Shake container well and apply liberally. Allow 1-2 minutes for Combat film to form. Repeat daily as necessary for up to 1 week. If there is no improvement consult your veterinarian. Combat should be used as a part of a routine footcare programme. Use in conjunction with regular footbathing with Provita Hoofsure Endurance.

Provita Eurotech Limited

21 Bankmore Road, Omagh,

Co. Tyrone, Northern Ireland, BT79 0EU Provita Animal Health LLC

4500 140TH Avenue North,

Suite 101, Clearwater, FL 33762

Tel: + (1) 727 431 9511

Email: info@provita-animalhealth.com www.provita-animalhealth.com

PRINCIPAL DISPLAY PANEL - 1 Litre Bottle Label

Provita
Animal Health Naturally

ANTIBIOTIC
FREE

Combat
Film-forming wound
and hoof spray

0.264 gal
(1 Litre)

100
Applications